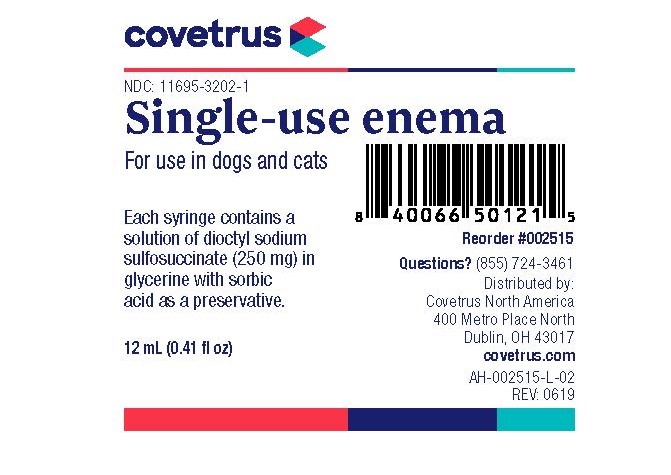 DRUG LABEL: Single-Use
NDC: 11695-3202 | Form: ENEMA
Manufacturer: Covetrus
Category: animal | Type: OTC ANIMAL DRUG LABEL
Date: 20251230

ACTIVE INGREDIENTS: DOCUSATE SODIUM 250 mg/12 mL

DESCRIPTION

Single-Use Enema

For Use in dogs and cats

DOSAGE FORMS AND STRENGTHS

Each syringe contains a solution of dioctyl sodium sulfosuccinate (250 mg) in glycerine with sorbic acid as a preservative.

PACKAGE LABEL

covetrus

NDC: 11695-3202-1

Single-use enema

For use in dogs and cats

Each syringe contains a solution of dioctyl sodium sulfosuccinate (250 mg) in glycerine with sorbic acid as a preservative.

Reorder #002515

12 mL (0.41 fl oz)

Questions? (855) 724-3461

Distributed by:

Covetrus North America

400 Metro Place North

Dublin, OH 43017

covetrus.com

AH-002515-L-02

Rev. 0619